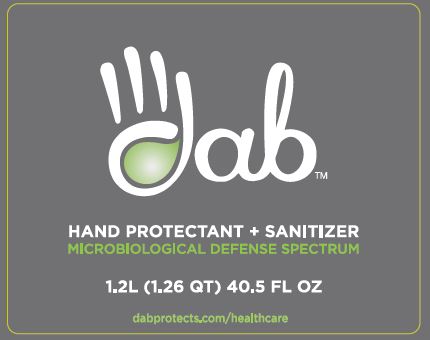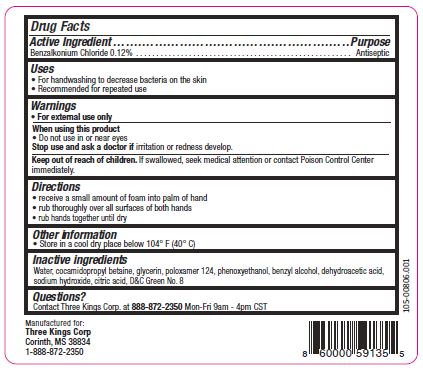 DRUG LABEL: DAB
NDC: 72898-001 | Form: SOLUTION
Manufacturer: Three Kings Corp
Category: otc | Type: HUMAN OTC DRUG LABEL
Date: 20200210

ACTIVE INGREDIENTS: BENZALKONIUM CHLORIDE 0.12 g/100 mL
INACTIVE INGREDIENTS: GLYCERIN; PHENOXYETHANOL; DEHYDROACETIC ACID; CITRIC ACID MONOHYDRATE; BENZYL ALCOHOL; SODIUM HYDROXIDE; WATER; COCAMIDOPROPYL BETAINE; POLOXAMER 124; D&C GREEN NO. 8

Active Ingredient

Benzalkonium Chloride 0.12%

Purpose

Antiseptic

Uses

- For handwashing to decrease bacteria on the skin
- Recommended for repeated use

Warnings

- For external use only

When using this product

- Do not use in or near eyes

Stop use and ask a doctor if irritation or redness develop.

Keep out of reach of children. If swallowed, seek medical attention or contact Poison Control Center immediately.

Directions

- receive a small amount of foam into palm of hand
- rub thoroughly over all surfaces of both hands
- rub hands together until dry

Other information

- Store in a cool dry place below 104 F (40 C)

Inactive ingredients

Water, cocamidopropyl betaine, glycerin, poloxamer 124, phenoxyethanol, benzyl alcohol, dehydroacetic acid, sodium hydroxide, citric acid, D&C Green No. 8

Questions?

Contact Three Kings Corp. at 888-872-2350 Mon-Fri 9 am - 4pm CST

PACKAGE LABEL

dab

HAND PROTECTANT + SANITIZER

MICROBIOLOGICAL DEFENSE SPECTRUM

1.2L (1.26 QT) 40.5 GL OZ

dapprotects.com/healthcare